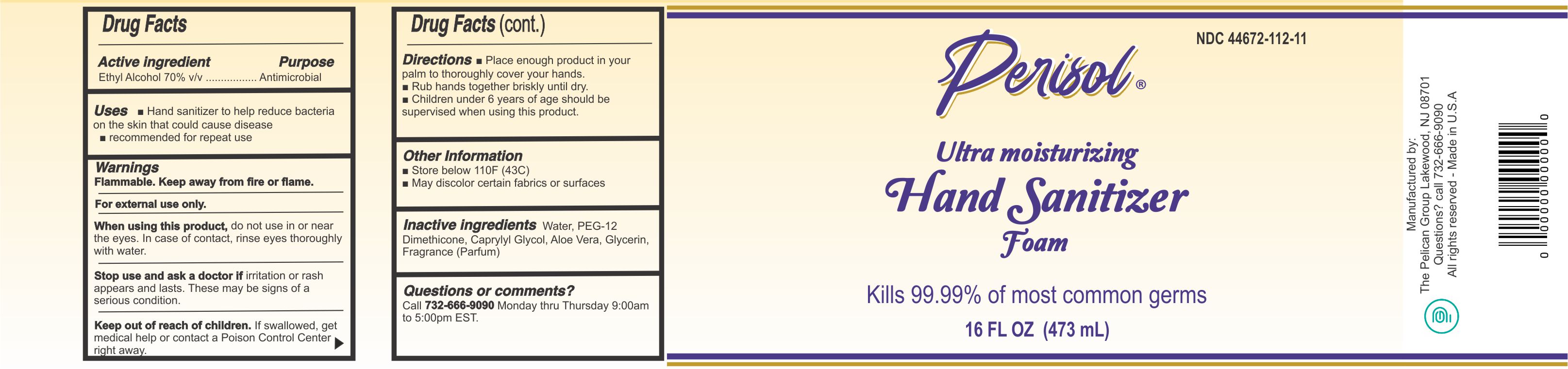 DRUG LABEL: Perisol Hand Sanitizer Foam
NDC: 44672-112 | Form: SOLUTION
Manufacturer: PELICAN GROUP LLC, THE
Category: otc | Type: HUMAN OTC DRUG LABEL
Date: 20210310

ACTIVE INGREDIENTS: ALCOHOL 80 mL/100 mL
INACTIVE INGREDIENTS: FRAGRANCE CLEAN ORC0600327; ALOE VERA LEAF; CAPRYLYL GLYCOL; GLYCERIN; PEG-12 DIMETHICONE (300 CST); WATER

Active Ingredient(s)

Alcohol 70% v/v. Purpose: Antimicrobial. Purpose: Antiseptic

Purpose

Antiseptic, Hand Sanitizer

Use

Hand Sanitizer to help reduce bacteria that potentially can cause disease. For use when soap and water are not available.

Warnings

- Flammable. Keep away from fire or flame.
- For external use only.

Do not use

- Keep out of reach of children. If swallowed, get medical help or contact a Poison Control Center right away.

When using this product keep out of eyes, ears, and mouth. In case of contact with eyes, rinse eyes thoroughly with water.

Stop use and ask a doctor if irritation or rash occurs. These may be signs of a serious condition.

Keep out of reach of children. If swallowed, get medical help or contact a Poison Control Center right away.

Directions

- Place enough product in your palm to thoroughly cover your hands. Rub hands together briskly until dry.
- Children under 6 years of age should be supervised when using this product.

Other information

- Store below 110F (43C)
- May discolor certain fabrics or surfaces

Inactive ingredients

Water, PEG-12 Dimethicone, Caprylyl Glycol, Aloe Vera, Glycerin, Fragrance (Parfum)

Package Label - Principal Display Panel

473.2mL NDC: 44672-112-11